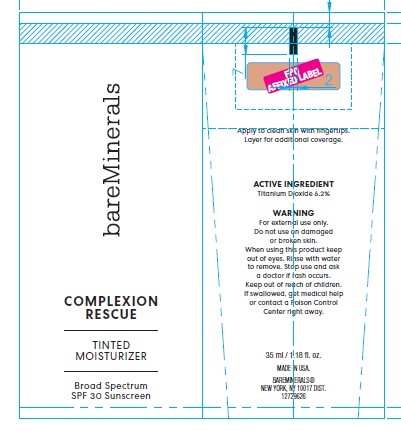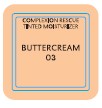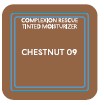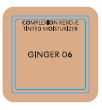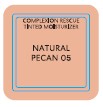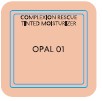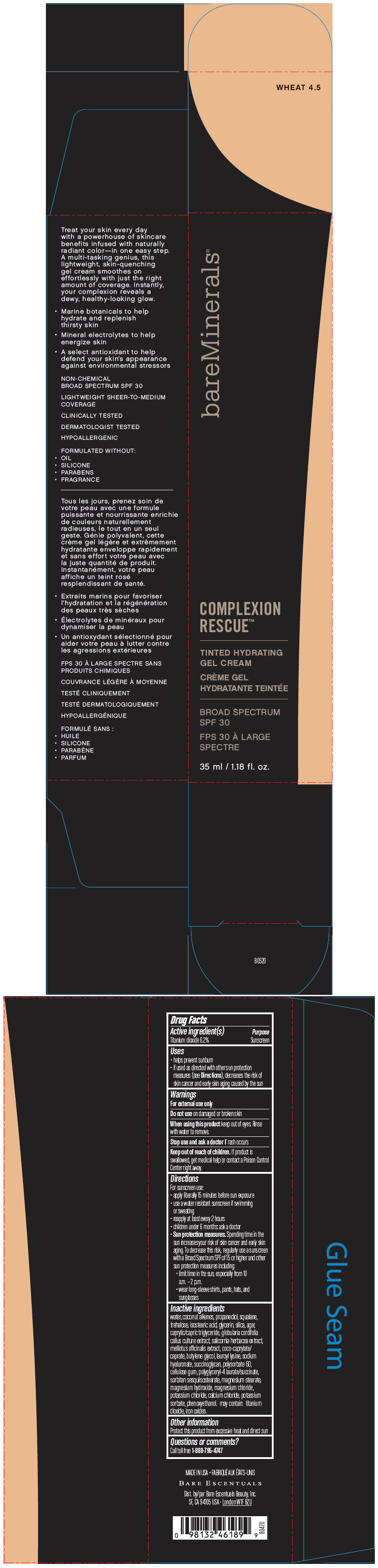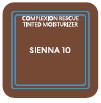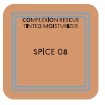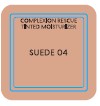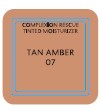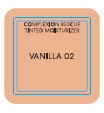 DRUG LABEL: bareMinerals Complexion Rescue Broad Spectrum SPF 30
NDC: 98132-751 | Form: LIQUID
Manufacturer: Orveon Global US, LLC
Category: otc | Type: HUMAN OTC DRUG LABEL
Date: 20231004

ACTIVE INGREDIENTS: TITANIUM DIOXIDE 62 mg/1 mL
INACTIVE INGREDIENTS: WATER; COCONUT ALKANES; PROPANEDIOL; SQUALANE; TREHALOSE; ISOSTEARIC ACID; GLYCERIN; SILICON DIOXIDE; AGAR; MEDIUM-CHAIN TRIGLYCERIDES; SALICORNIA EUROPAEA; COCO-CAPRYLATE/CAPRATE; BUTYLENE GLYCOL; LAUROYL LYSINE; HYALURONATE SODIUM; POLYSORBATE 60; CARBOXYMETHYLCELLULOSE SODIUM; MAGNESIUM STEARATE; MAGNESIUM HYDROXIDE; MAGNESIUM CHLORIDE; POTASSIUM CHLORIDE; CALCIUM CHLORIDE; POTASSIUM SORBATE; PHENOXYETHANOL; FERRIC OXIDE RED

bareMinerals ® Complexion Rescue™ Broad Spectrum SPF 30

Drug Facts

Active ingredient(s)

Titanium dioxide 6.2%

Purpose

Sunscreen

Uses

- helps prevent sunburn
- if used as directed with other sun protection measures (see Directions), decreases the risk of skin cancer and early skin aging caused by the sun

Warnings

For external use only

Do not use on damaged or broken skin

When using this product keep out of eyes. Rinse with water to remove.

Stop use and ask a doctor if rash occurs

Keep out of reach of children. If product is swallowed, get medical help or contact a Poison Control Center right away.

Directions

For sunscreen use:

- apply liberally 15 minutes before sun exposure
- use a water resistant sunscreen if swimming or sweating
- reapply at least every 2 hours
- children under 6 months: ask a doctor
- Sun protection measures. Spending time in the sun increases your risk of skin cancer and early skin aging. To decrease this risk, regularly use a sunscreen with a Broad Spectrum SPF of 15 or higher and other sun protection measures including:
  - limit time in the sun, especially from 10 a.m. – 2 p.m.
  - wear long-sleeve shirts, pants, hats, and sunglasses

Inactive ingredients

water, coconut alkanes, propanediol, squalane, trehalose, isostearic acid, glycerin, silica, agar, caprylic/capric triglyceride, globularia cordifolia callus culture extract, salicornia herbacea extract, melilotus officinalis extract, coco-caprylate/caprate, butylene glycol, lauroyl lysine, sodium hyaluronate, succinoglycan, polysorbate 60, cellulose gum, polyglyceryl-4 laurate/succinate, sorbitan sesquiisostearate, magnesium stearate, magnesium hydroxide, magnesium chloride, potassium chloride, calcium chloride, potassium sorbate, phenoxyethanol. may contain: titanium dioxide, iron oxides.

Other information

Protect this product from excessive heat and direct sun

Questions or comments?

Call toll free 1-888-795-4747

Dist. by Bare Escentuals Beauty, Inc., SF, CA 94105 USA

PRINCIPAL DISPLAY PANEL - 35 ml Bottle Box - OPAL 01

bareMinerals®

COMPLEXION
RESCUE™

TINTED HYDRATING
GEL CREAM

BROAD SPECTRUM
SPF 30

35 ml / 1.18 fl. oz.

PRINCIPAL DISPLAY PANEL - 35 ml Bottle Box - VANILLA 02

bareMinerals®

COMPLEXION
RESCUE™

TINTED HYDRATING
GEL CREAM

BROAD SPECTRUM
SPF 30

35 ml / 1.18 fl. oz.

PRINCIPAL DISPLAY PANEL - 35 ml Bottle Box - BUTTERCREAM 03

bareMinerals®

COMPLEXION
RESCUE™

TINTED HYDRATING
GEL CREAM

BROAD SPECTRUM
SPF 30

35 ml / 1.18 fl. oz.

PRINCIPAL DISPLAY PANEL - 35 ml Bottle Box - SUEDE 04

bareMinerals®

COMPLEXION
RESCUE™

TINTED HYDRATING
GEL CREAM

BROAD SPECTRUM
SPF 30

35 ml / 1.18 fl. oz.

PRINCIPAL DISPLAY PANEL - 35 ml Bottle Box - NATURAL 05

bareMinerals®

COMPLEXION
RESCUE™

TINTED HYDRATING
GEL CREAM

BROAD SPECTRUM
SPF 30

35 ml / 1.18 fl. oz.

PRINCIPAL DISPLAY PANEL - 35 ml Bottle Box - GINGER 06

bareMinerals®

COMPLEXION
RESCUE™

TINTED HYDRATING
GEL CREAM

BROAD SPECTRUM
SPF 30

35 ml / 1.18 fl. oz.

PRINCIPAL DISPLAY PANEL - 35 ml Bottle Box - TAN 07

bareMinerals®

COMPLEXION
RESCUE™

TINTED HYDRATING
GEL CREAM

BROAD SPECTRUM
SPF 30

35 ml / 1.18 fl. oz.

PRINCIPAL DISPLAY PANEL - 35 ml Bottle Box - SPICE 08

bareMinerals®

COMPLEXION
RESCUE™

TINTED HYDRATING
GEL CREAM

BROAD SPECTRUM
SPF 30

35 ml / 1.18 fl. oz.

PRINCIPAL DISPLAY PANEL - 35 ml Bottle Box - CHESTNUT 09

bareMinerals®

COMPLEXION
RESCUE™

TINTED HYDRATING
GEL CREAM

BROAD SPECTRUM
SPF 30

35 ml / 1.18 fl. oz.

PRINCIPAL DISPLAY PANEL - 35 ml Bottle Box - SIENNA 10

bareMinerals®

COMPLEXION
RESCUE™

TINTED HYDRATING
GEL CREAM

BROAD SPECTRUM
SPF 30

35 ml / 1.18 fl. oz.